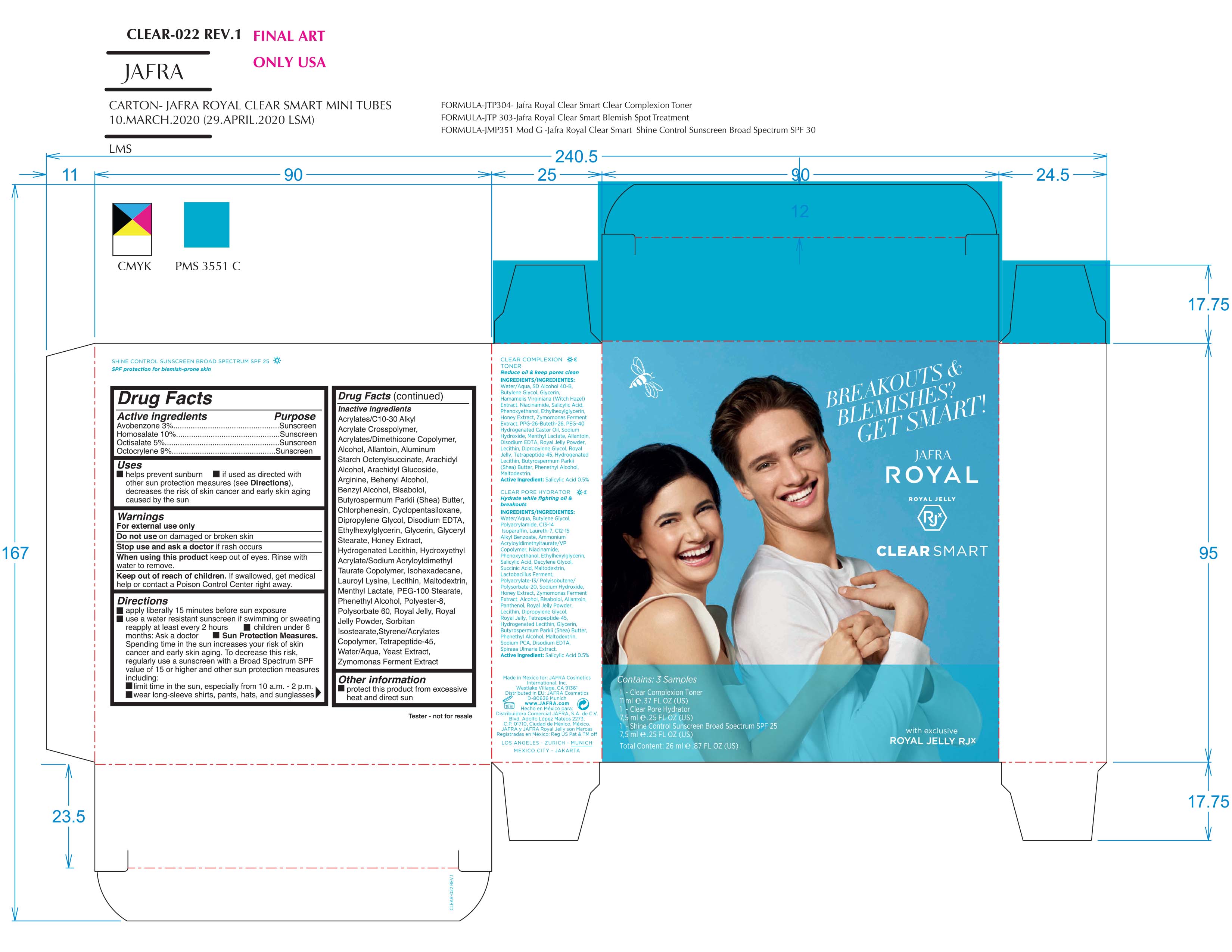 DRUG LABEL: Shine Control Sunscreen Broad Spectrum SPF 50
NDC: 68828-291 | Form: KIT | Route: TOPICAL
Manufacturer: Jafra cosmetics International
Category: otc | Type: HUMAN OTC DRUG LABEL
Date: 20200602

ACTIVE INGREDIENTS: AVOBENZONE 3 g/100 mL; OCTOCRYLENE 9 g/100 mL; OCTISALATE 5 g/100 mL; HOMOSALATE 10 g/100 mL
INACTIVE INGREDIENTS: ALUMINUM STARCH OCTENYLSUCCINATE; PEG-100 STEARATE; SORBITAN ISOSTEARATE; CHLORPHENESIN; ROYAL JELLY; WATER; DIPROPYLENE GLYCOL; ETHYLHEXYLGLYCERIN; POLYSORBATE 60; CARBOMER INTERPOLYMER TYPE A (ALLYL SUCROSE CROSSLINKED); BENZYL ALCOHOL; HYDROGENATED SOYBEAN LECITHIN; ISOHEXADECANE; PHENYLETHYL ALCOHOL; POLYESTER-8 (1400 MW, CYANODIPHENYLPROPENOYL CAPPED); YEAST, UNSPECIFIED; ARGININE; LEVOMENOL; ARACHIDYL GLUCOSIDE; LECITHIN, SOYBEAN; CYCLOMETHICONE 5; GLYCERIN; GLYCERYL MONOSTEARATE; HYDROXYETHYL ACRYLATE/SODIUM ACRYLOYLDIMETHYL TAURATE COPOLYMER (100000 MPA.S AT 1.5%); ALCOHOL; ALLANTOIN; DOCOSANOL; ARACHIDYL ALCOHOL; SHEA BUTTER; EDETATE DISODIUM; MALTODEXTRIN; MENTHYL LACTATE, (-)-; HONEY; LAUROYL LYSINE

Clear Smart Royal Jelly Sample Set

Active Ingredients Purpose

Avobennzone 3% Sunscreen

Homosalate 10% Sunscreen

Octisalate 5% Sunscreen

Octocrylene 9% Sunscreen

Uses

- Helps Prevent Sunburn
- If used as directed with other sun protection measures (see Directions), decreases the risk of skin cancer and early skin aging caused by the sun.

Keep out of reach of children. If product is swallowed, get medical help or contact a poison Control Center right away

Stop use and ask a doctor if rash occurs

Warnings

- For external use only
- Do not use on damaged or broken skin
- When using this product keep out of eyes. Rinse with water to remove

Directions

Apply liberally 15 minutes before sun exposure
Use a water-resistant sunscreen if swimming or sweating
Reapply at least every 2 hours.

Children under 6 months of age: ask a doctor.
Sun Protection Measures Spending time in the sun increases your risk of
skin cancer and early skin aging. To decrease this risk, regularly use a
sunscreen with a Broad-Spectrum SPF value of 15 or higher and other sun
protection measures including: • limit your time in the sun, especially from 10
a.m. – 2 p.m. • wear long-sleeved shirts, pants, hats, and sunglasses

INACTIVE INGREDIENT

Acrylates/C10-30 Alkyl Acrylate Crosspolymer, Acrylates/Dimethicone Copolymer, Alcohol, Allantoin, Aluminum Starch Octenylsuccinate, Arachidyl Alcohol, Arachidyl Glucoside, Arginine, Behenyl Alocohol, Benzyl Alcohol, Bisabolol, Butyrospermum Parkii (Shea) Butter, Chlorphenesin, Cyclopentasiloxane, Dipropylene Glycol, Disodium EDTA, Ethylhexylglycerin, Glycerin, Glyceryl Stearate, Honey Extract, Hydrogenated Lecithin, Hydroxyethyl Acrylate/Sodium Acryloyldimethyl Taurate Copolymer, Isohexadecane, Lauroyl Lysine, Lecithin, Maltodextrin, Menthyl Lactate, PEG-100 Stearate, Phenethyl Alcohol, Polyester-8, Polysorbate 60, Royal Jelly, Royal Jelly Powder, Sorbitan Isostearate, Styrene/Acrylates Copolymer, Tetrapeptide-45, Water/Aqua, Yeast Extract, Zymomonas Ferment Extract

PACKAGE LABEL

Jafra

Royal

Royal Jelly

Clear Smart

Contains: 3 samples

1 - Clear Complexion Toner

11ml .37 FL OZ (US)

1 - Clear Pore Hydrator

7,5 ml .25 FL OZ (US)

1 - Shine Control Sunscreen Broad Spectrum SPF 25

7,5 ml .25 FL OZ (US)

Total content: 26 ml .87 FL OZ (US)